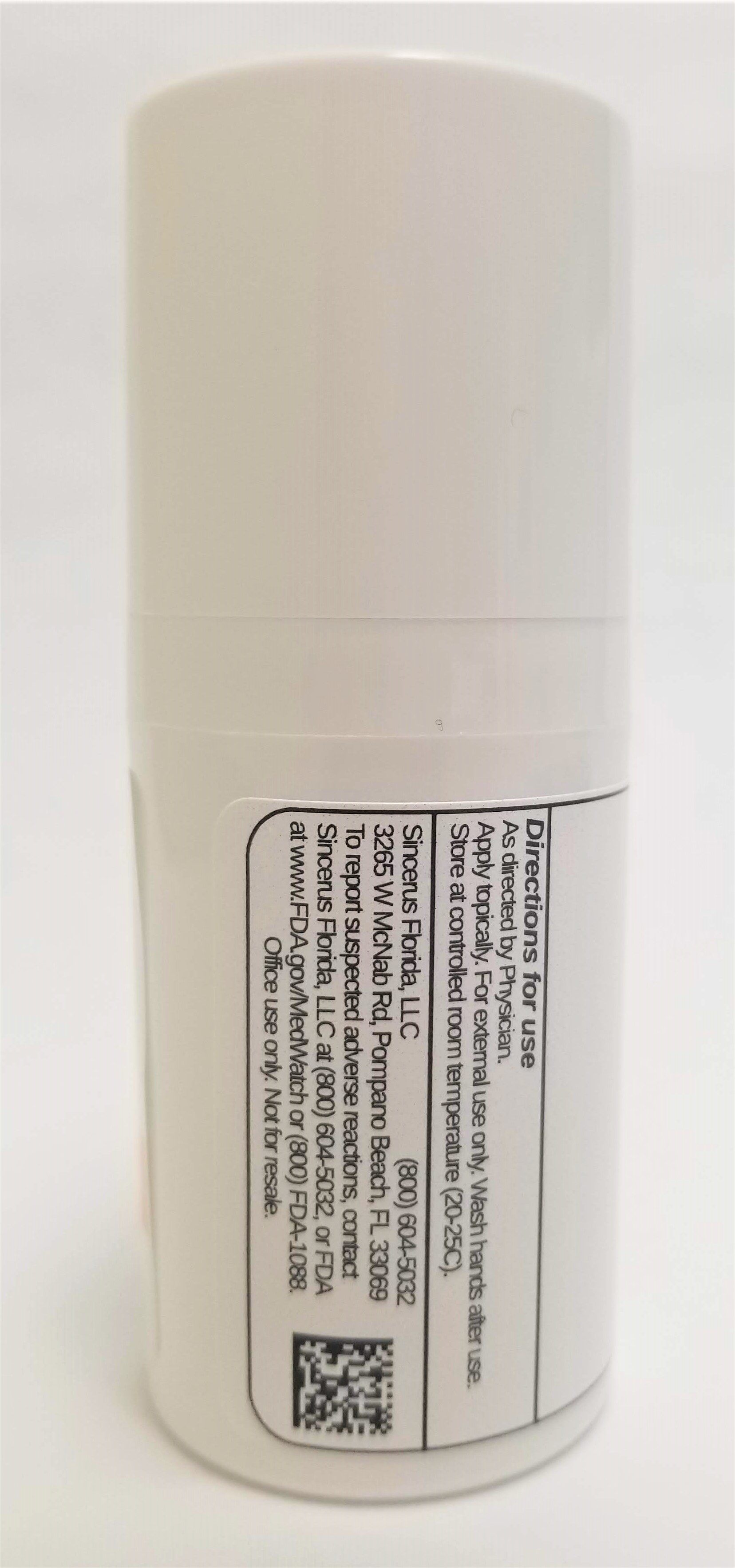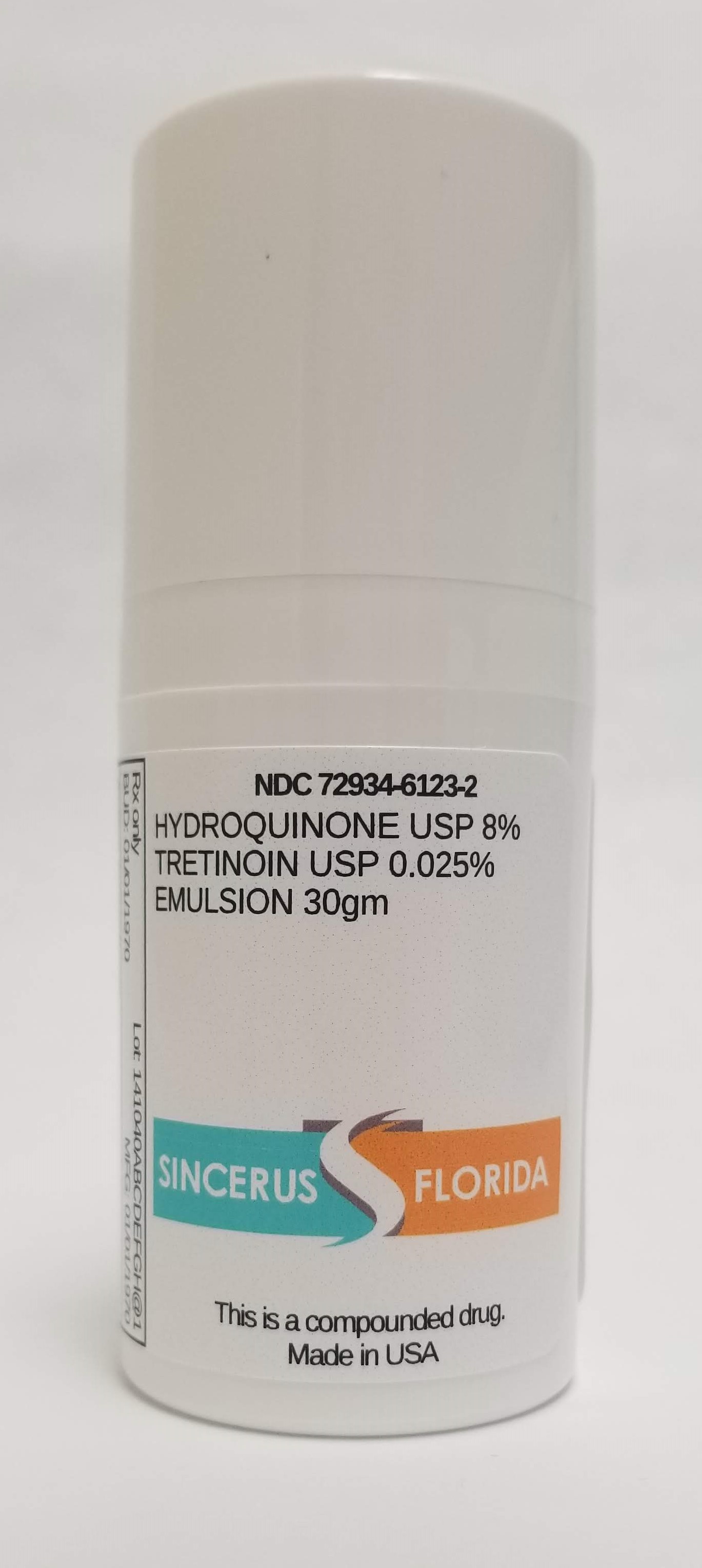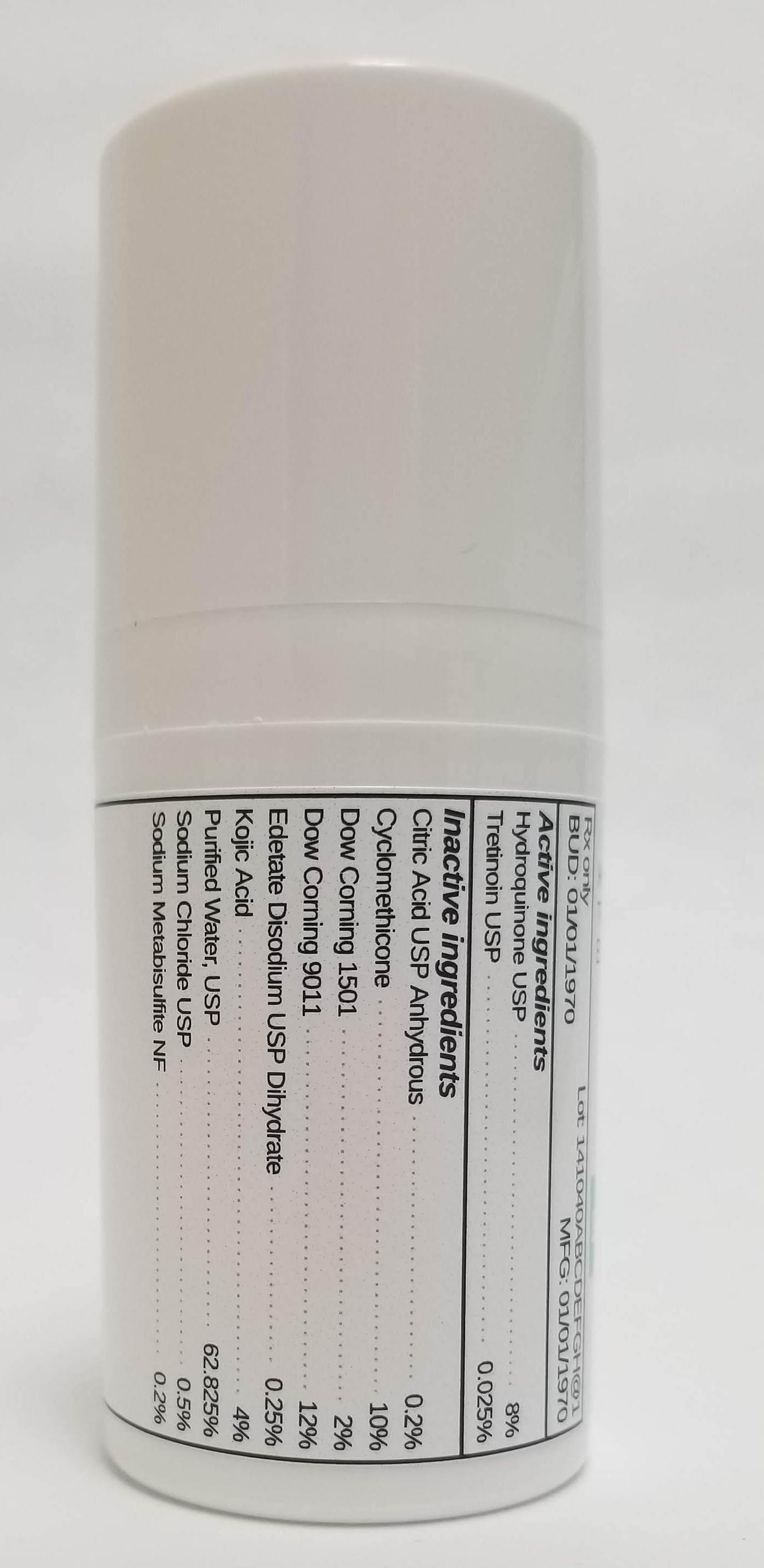 DRUG LABEL: HYDROQUINONE 8%  / TRETINOIN 0.025%
NDC: 72934-6123 | Form: EMULSION
Manufacturer: Sincerus Florida, LLC
Category: prescription | Type: HUMAN PRESCRIPTION DRUG LABEL
Date: 20190520

ACTIVE INGREDIENTS: TRETINOIN 0.025 g/100 g; HYDROQUINONE 8 g/100 g

HYDROQUINONE 8% / TRETINOIN 0.025%